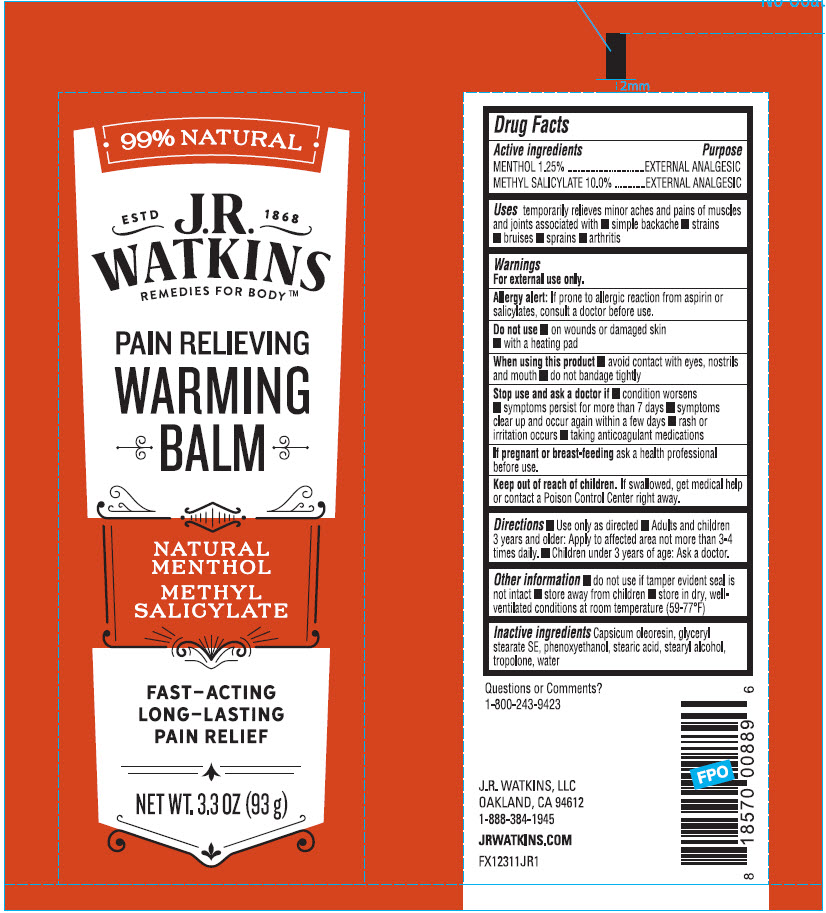 DRUG LABEL: Pain Relieving Warming Balm
NDC: 72342-030 | Form: GEL
Manufacturer: J.R. Watkins, LLC.
Category: otc | Type: HUMAN OTC DRUG LABEL
Date: 20240208

ACTIVE INGREDIENTS: METHYL SALICYLATE 10 g/100 g; MENTHOL, UNSPECIFIED FORM 1.25 g/100 g
INACTIVE INGREDIENTS: WATER; GLYCERYL STEARATE SE; STEARIC ACID; PHENOXYETHANOL; TROPOLONE; CAPSICUM OLEORESIN; STEARYL ALCOHOL

Pain Relieving Warming Balm

Drug Facts

ACTIVE INGREDIENT

Active Ingredients | Purpose
MENTHOL 1.25% | EXTERNAL ANALGESIC
METHYL SALICYLATE 10.0% | EXTERNAL ANALGESIC

Uses

temporarily relieves minor aches and pains of muscles and joints associated with

- simple backache
- strains
- bruises
- sprains
- arthritis

Warnings

For external use only.

Allergy alert

If prone to allergic reaction form aspiring or salicylates, consult a doctor before use.

Do not use

- on wounds or damaged skin
- with a heading pad

When using this product

- avoid contact with eyes, nostrils and mouth
- do not bandage tightly

Stop use and ask a doctor if

- condition worsens
- symptoms persist for more than 7 days
- symptoms clear up and occur again within a few days
- rash or irritation occurs
- taking anticoagulant medications

PREGNANCY OR BREAST FEEDING

If pregnant or breast-feedingask a health professional before use

Keep out of reach of children.If swallowed, get medical help or contact a Poison Control Center right away.

Directions

- Use only as directed
- Adults and children 3 years and older: Apply to affected area not more than 3-4 times daily.
- Children under 3 years of age: Ask a doctor.

Other information

- do not use if tamper evident seal is not intact
- store away from children
- store in dry, well-ventilated conditions at room temperature (59-77°F)

Inactive ingredients

Capsicum oleoresin, glyceryl stearate SE, phenoxyethanol, stearic acid, stearyl alcohol, tropolone, water

Questions or Comments?

1-800-243-9423

PRINCIPAL DISPLAY PANEL - 93 g Tube Label

99% NATURAL

ESTD J.R. 1868
WATKINS
REMEDIES FOR BODY™

PAIN RELIEVING
WARMING
BALM

NATURAL
MENTHOL

METHYL
SALICYLATE

FAST–ACTING
LONG–LASTING
PAIN RELIEF

NET WT. 3.3 OZ (93 g)